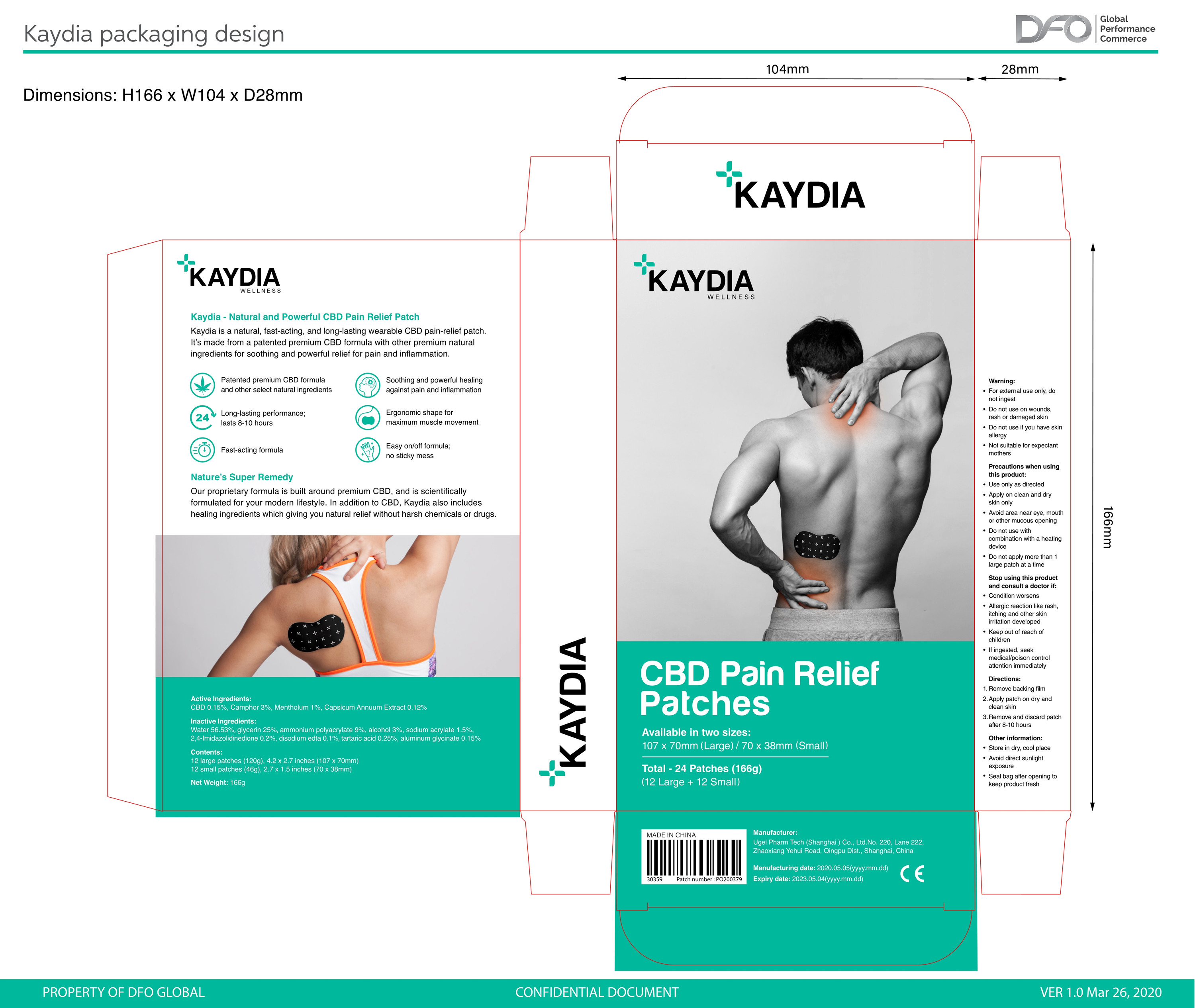 DRUG LABEL: Kaydia Patch
NDC: 75140-002 | Form: PATCH
Manufacturer: STRONG CURRENT ENTERPRISES LIMITED
Category: otc | Type: HUMAN OTC DRUG LABEL
Date: 20200501

ACTIVE INGREDIENTS: CAMPHOR (NATURAL) 3 g/100 g; LEVOMENTHOL 1 g/100 g; CANNABIDIOL 0.15 g/100 g
INACTIVE INGREDIENTS: WATER; TARTARIC ACID; DIHYDROXYALUMINUM AMINOACETATE; ALCOHOL; HYDANTOIN; GLYCERIN; SODIUM ACRYLATE; DISODIUM EDTA-COPPER CU-64

Kaydia Patch

Active Ingredients

CBD 0.15%, Camphor 3%, Mentholum 1%, Capsicum Annuum Extract 0.12%

Warning

For external use only, do not ingest
Do not use on wounds,rash or damaged skin
Do not use if you have skin allergy
Not suitable for expectant mothers

when using this product

Use only as directed
Apply on clean and dry skin only
Avoid area near eye, mouth or other mucous opening
Do not use with combination with a heating device
Do not apply more than 1 large patch at a time

STOP USE

Stop using this product and consult a doctor if:Condition worsens
Allergic reaction like rash, itching and other skin irritation developed
Keep out of reach of children
If ingested, seek medical/poison control attention immediately

Directions

1.Remove backing film
2.Apply patch on dry and clean skin
3.Remove and discard patch after 8-10 hours

Other information

Store in dry, cool place
Avoid direct sunlight exposure
Seal bag after opening to keep product fresh

Inactive Ingredients

Water 56.53%, glycerin 25%, ammonium polyacrylate 9%, alcohol 3%, sodium acrylate 1.5%, 2,4-Imidazolidinedione 0.2%, disodium edta 0.1%, tartaric acid 0.25%, aluminum glycinate 0.15%